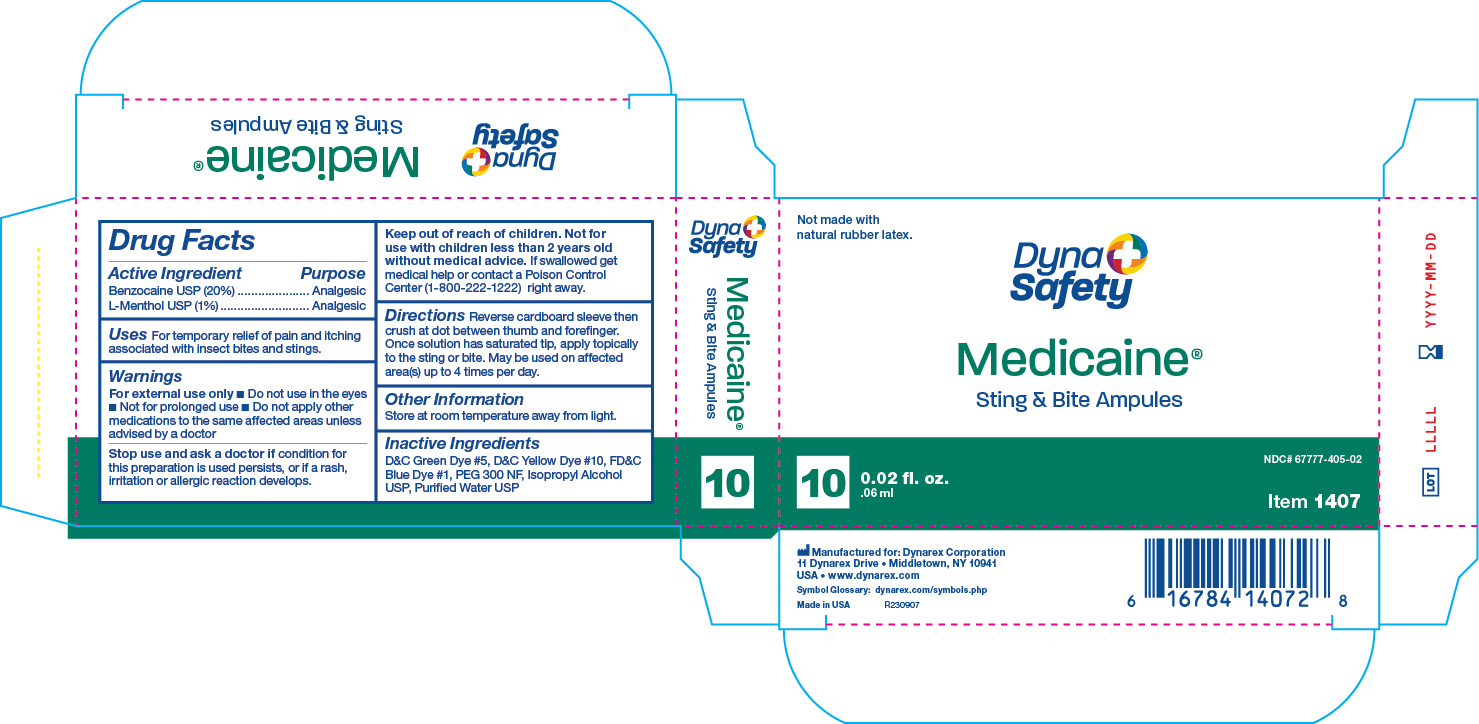 DRUG LABEL: Medicaine Sting and Bite
NDC: 67777-405 | Form: SWAB
Manufacturer: Dynarex Corporation
Category: otc | Type: HUMAN OTC DRUG LABEL
Date: 20240624

ACTIVE INGREDIENTS: BENZOCAINE 0.12 g/0.6 mL
INACTIVE INGREDIENTS: MENTHOL

1407 Medicaine Insect Bite (Ampule) 67777-405-01

Active Ingredient

Benzocaine USP 20%

Purpose

Analgesic

Active Ingredient

L-Menthol USP 1%

Purpose

Analgesic

Use(s)

For the temporary relief of pain and itching associated with insect bites and stings.

Warnings

For External Use Only

When Using Section

• Do not use in the eyes

• Not for prolonged use

• Do not apply other medication to the same affected areas unless advised by a doctor

Stop use and ask a doctor if

Condition persists, or if a rash, irritation, or allergic reaction develops.

Keep out of reach of children

If swallowed get medical help or contact a Poison Control Center (1-800-222-1222) right away.

Directions

Reverse cardboard sleeve then crush at dot between thumb and forefinger. Once solution has saturated tip, apply topically to the sting or bit. May be used on affected area(s) up to 4 times per day

Not for use with children less than 2 years old without medical advise.

Other Information

Store at room temperature 15º-30ºC (59º-86ºF) away from light.

Inactive Ingredients

D&C Green Dye #5, D&C Yellow Dye #10, FD&C Blue Dye #1, Isopropyl Alcohol, PEG 300 NF, Purified Water USP

Label

1407 Medicaine Sting and Bite Ampule